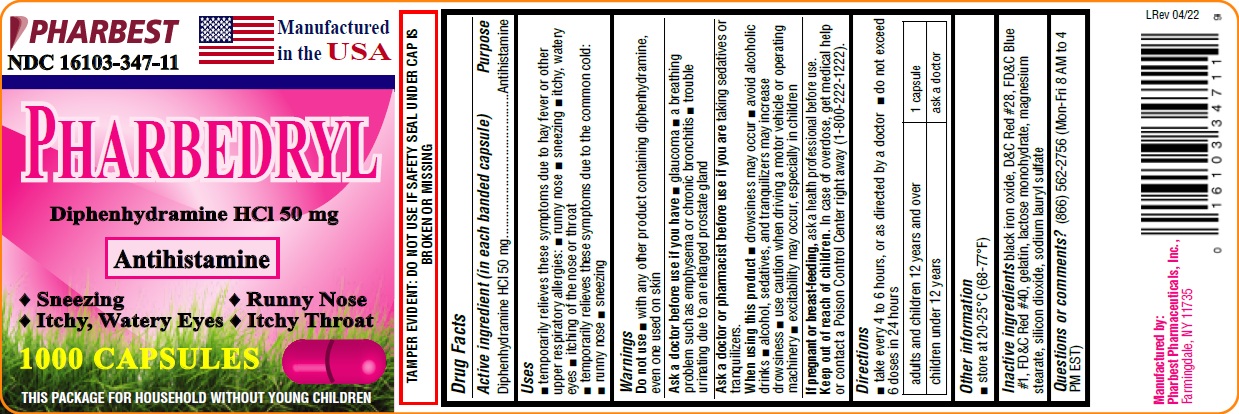 DRUG LABEL: PHARBEDRYL
NDC: 16103-347 | Form: CAPSULE
Manufacturer: Pharbest Pharmaceuticals, Inc.
Category: otc | Type: HUMAN OTC DRUG LABEL
Date: 20251224

ACTIVE INGREDIENTS: DIPHENHYDRAMINE HYDROCHLORIDE 50 mg/1 1
INACTIVE INGREDIENTS: FERROSOFERRIC OXIDE ; D&C RED NO. 28; FD&C BLUE NO. 1; FD&C RED NO. 40; GELATIN; LACTOSE MONOHYDRATE; MAGNESIUM STEARATE; SILICON DIOXIDE; SODIUM LAURYL SULFATE 

Drug Facts

Active ingredient (in each capsule)

Diphenhydramine HCl 50mg

Purpose

Antihistamine

Uses

- temporarily relieves these symptoms due to hay fever or other upper respiratory allergies:
- sneezing
- itching of the nose or throat
- runny nose
- itchy, watery eyes
- Temporarily relieves these symptoms due to common cold:
- runny nose
- sneezing

Warnings

Do not use

- with any other product containing diphenhydramine, even one used on skin

Ask a doctor before use if you have

- trouble urinating due to an enlarged prostate gland
- a breathing problem such as emphysema or chronic bronchitis
- glaucoma

Ask a doctor or pharmacist before use if you are

taking sedatives or tranquilizers

When using this product

- avoid alcoholic drinks
- drowsiness may occur
- excitability may occur, especially in children
- alcohol, sedatives & tranquilizers may increase drowsiness
- use caution when driving a motor vehicle or operating machinery

If pregnant or breast-feeding,

ask a health professional before use.

Keep out of reach of children.

In case of overdose, get medical help or contact a Poison Control Center right away (1-800-222-1222).

Directions

- take every 4-6 hours or as directed by a doctor
- do not exceed 6 doses in 24 hours.

Adults and children 12 years and over | 1 capsule
Children under 12 years of age | Ask a doctor

Other information

- store at 20°-25°C (68-77°F)

Inactive ingredients

black iron oxide, D & C red #28, FD & C blue #1, FD & C red #40, gelatin, lactose monohydrate, magnesium stearate, silicon dioxide, sodium lauryl sulfate

Questions or comments?

(866)562-2756 (Mon - Fri 8 AM to 4 PM EST)

PACKAGE LABEL

PHARBEST

NDC 16103-0347-11

Manufactured in the USA

PHARBEDRYL

Diphenhydramine HCl 50mg

Antihistamine

• Sneezing • Runny Nose

• Itchy, Watery Eyes • Itchy Throat

1000 CAPSULES

THIS PACKAGE FOR HOUSEHOLD WITHOUT YOUNG CHILDERN